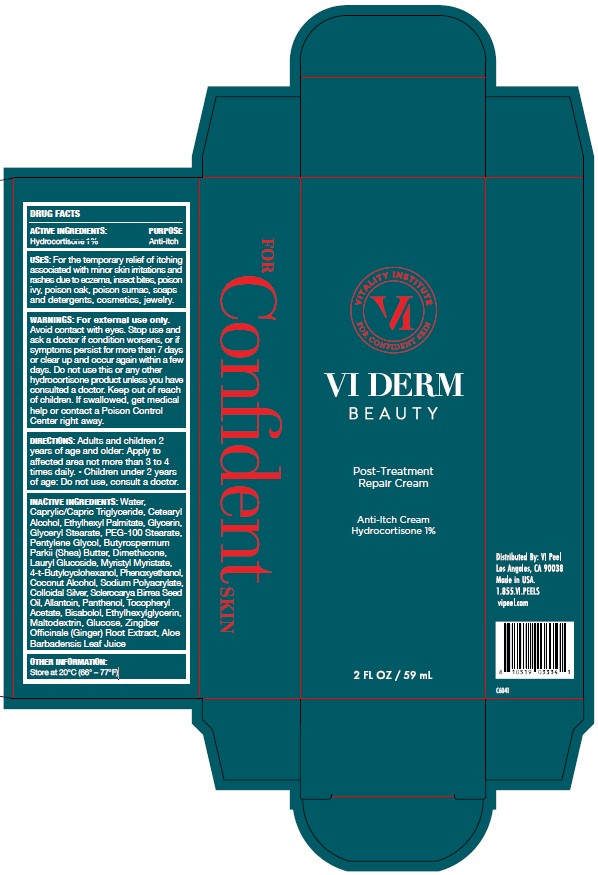 DRUG LABEL: Post Treatment Repair Cream
NDC: 67923-105 | Form: CREAM
Manufacturer: Vege Labs LLC.
Category: otc | Type: HUMAN OTC DRUG LABEL
Date: 20250312

ACTIVE INGREDIENTS: HYDROCORTISONE ACETATE 1 mg/100 mg
INACTIVE INGREDIENTS: CETEARYL ALCOHOL; PHENOXYETHANOL; COCONUT ALCOHOL; GLUCOSE; ALOE BARBADENSIS LEAF JUICE; SODIUM POLYACRYLATE (8000 MW); WATER; MALTODEXTRIN; LAURYL GLUCOSIDE; PEG-100 STEARATE; BUTYROSPERMUM PARKII (SHEA) BUTTER; ETHYLHEXYL PALMITATE; DIMETHICONE; MYRISTYL MYRISTATE; COLLOIDAL SILVER; SCLEROCARYA BIRREA SEED OIL; GINGER; ALLANTOIN; PANTHENOL; CAPRYLIC/CAPRIC TRIGLYCERIDE; .ALPHA.-TOCOPHEROL ACETATE, DL-; GLYCERYL STEARATE; PENTYLENE GLYCOL; 4-T-BUTYLCYCLOHEXANOL; GLYCERIN; BISABOLOL; ETHYLHEXYLGLYCERIN

ACTIVE INGREDIENTS

Hydrocortisone 1%

PURPOSE

Anti-itch

USES

For the temporary relief of itching associated with minor skin irritations and rashes due to eczema, insect bites, poison ivy, poison oak, poison sumac, soaps and detergents, cosmetics, jewelry.

WARNIGS

For external use only. Avoid contact with eyes. Stop use and ask a doctor if condition worsens, or if symptoms persist for more than 7 days or clear up and occur again within a few days. Do not use this or any other hydrocortisone product unless you have consulted a doctor.

DIRECTIONS

Adults and children 2 years of age and older: Apply to affected area not more than 3 to 4 times daily. - Children under 2 years of age: Do not use, consult a doctor.

INACTIVE INGREDIENTS

Water, Caprylic/Capric Triglyceride, Cetearyl Alcohol, Ethylhexyl Palmitate, Glycerin, Glyceryl Stearate, PEG-100 Stearate, Pentylene Glycol, Butyrospermum Parkii (Shea) Butter, Dimethicone, Lauryl Glucoside, Myristyl Myristate, 4-t-Butylcyclohexanol, Phenoxyethanol, Coconut Alcohol, Sodium Polyacrylate, Colloidal Silver, Sclerocarya Birrea Seed Oil, Allantoin, Panthenol, Tocopheryl Acetate, Bisabolol, Ethylhexylglycerin, Maltodextrin, Glucose, Zingiber Officinale (Ginger) Root Extract, Aloe Barbadensis Leaf Juice

OTHER INFORMATION

Store at 20°C (66° – 77°F)

Keep out of reach of children.

If swallowed, get medical help or contact Poison Control Center right away